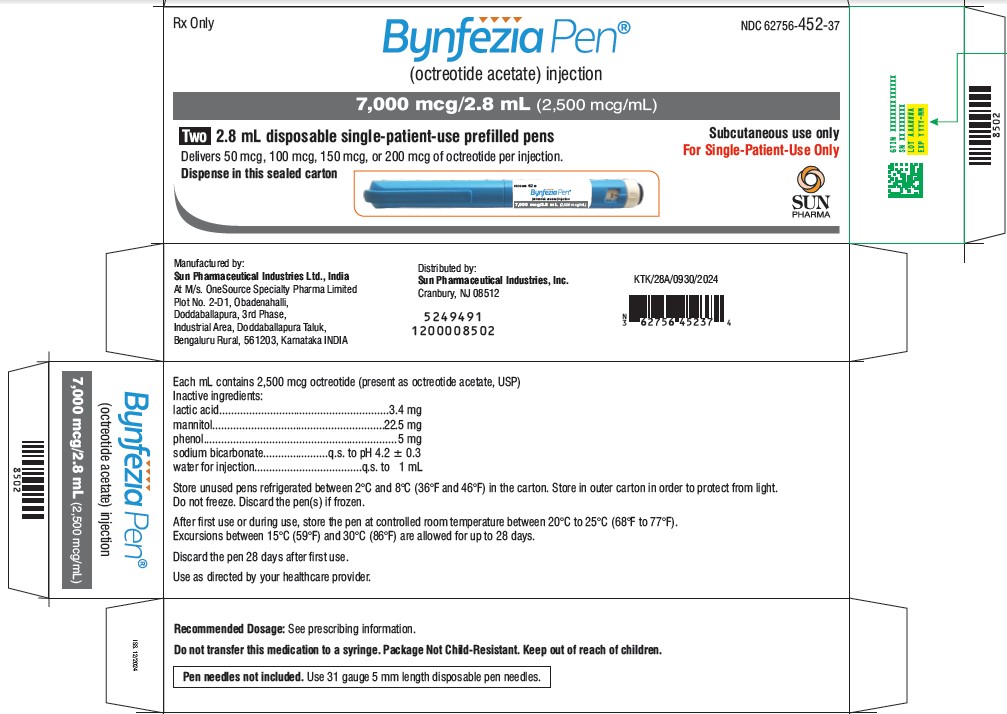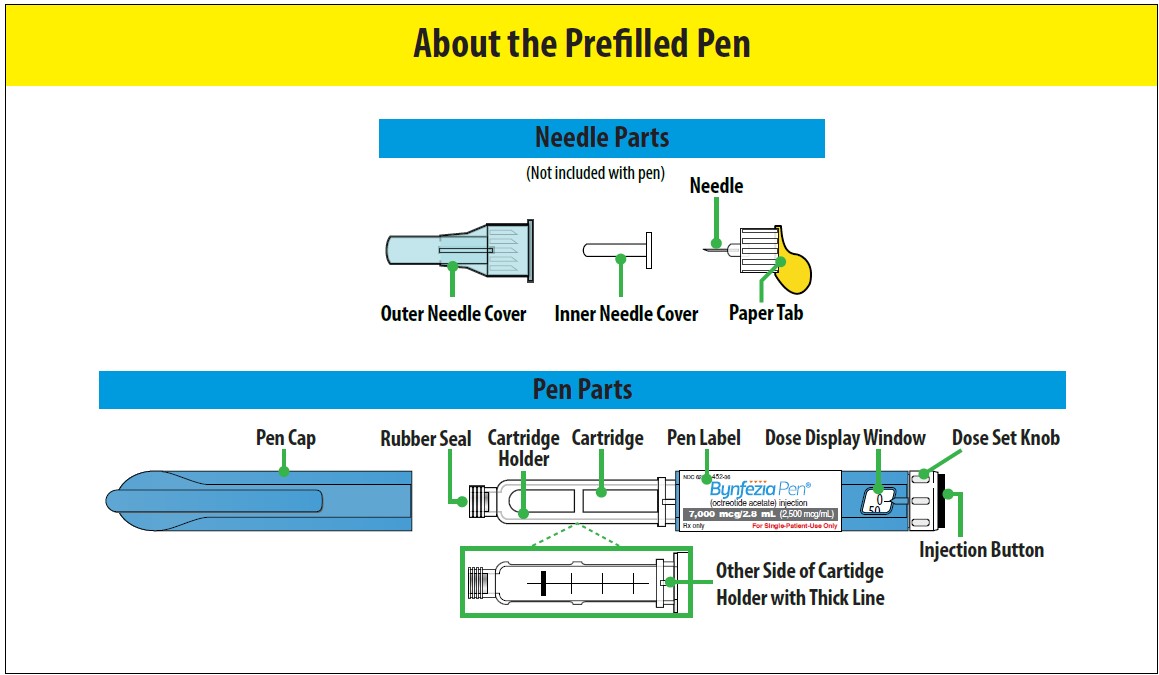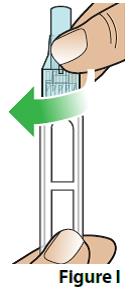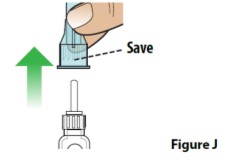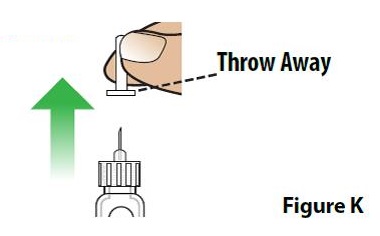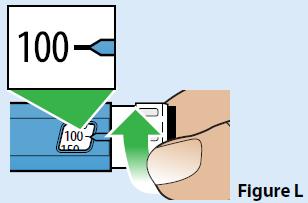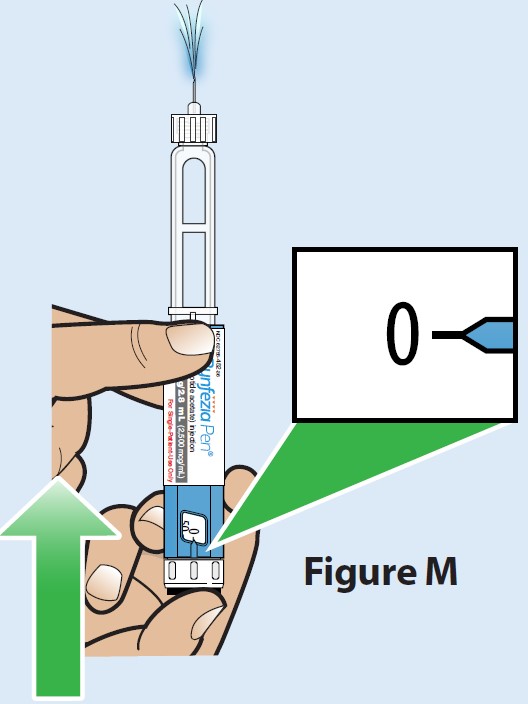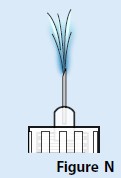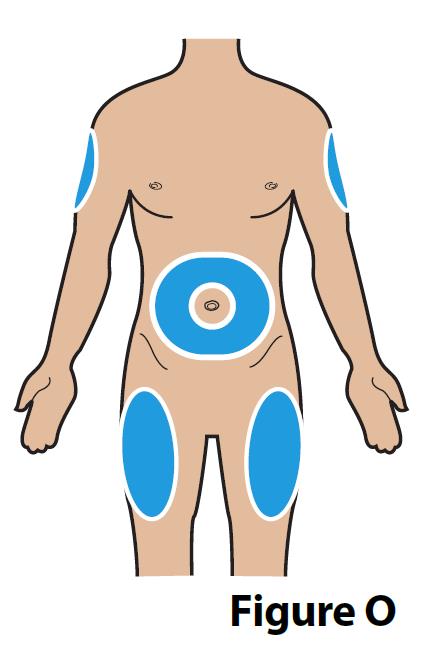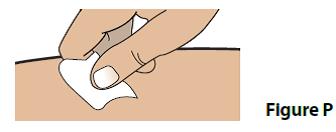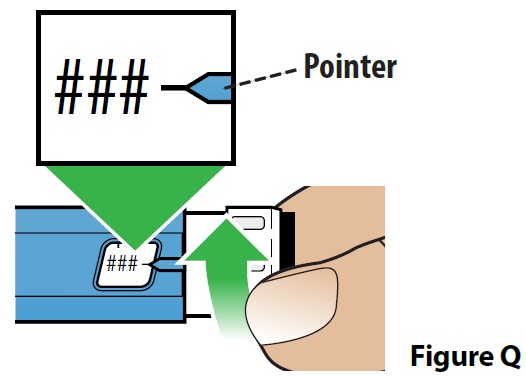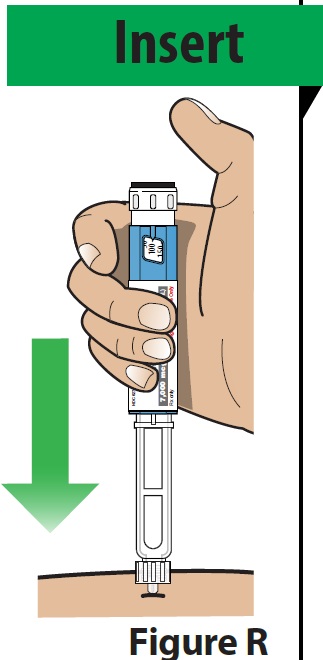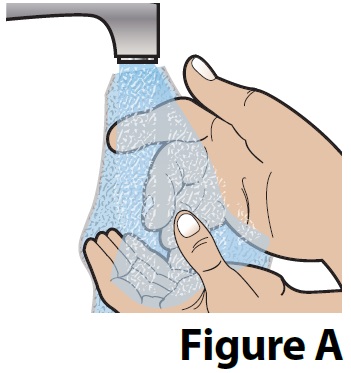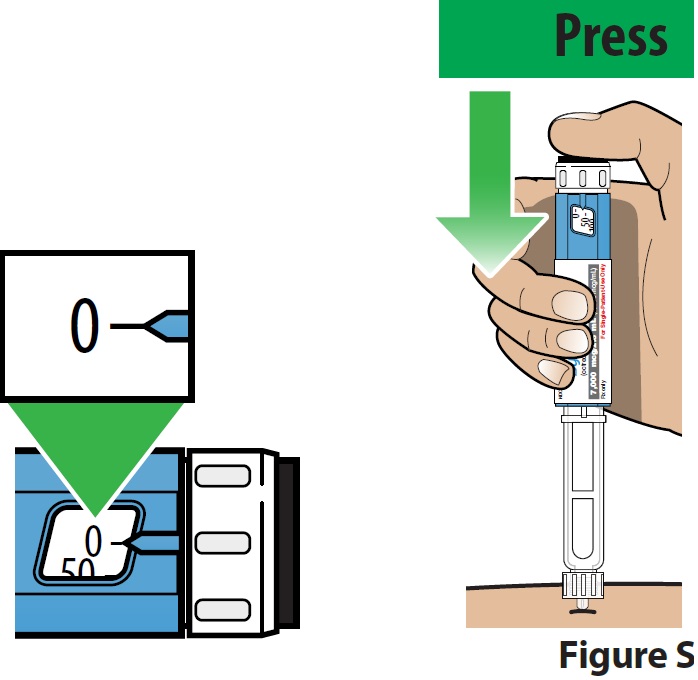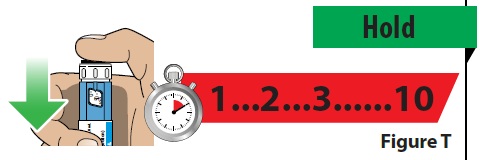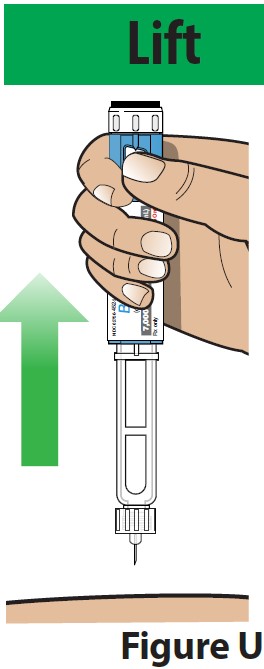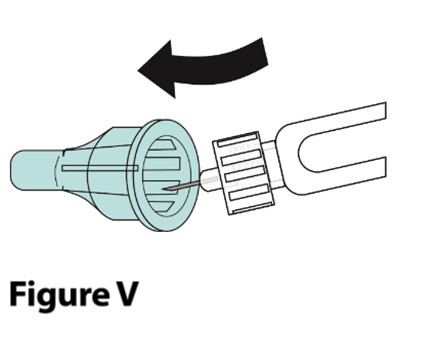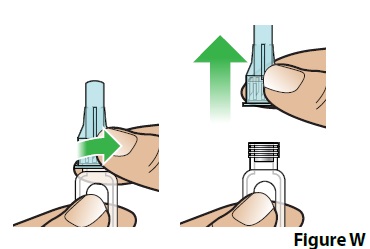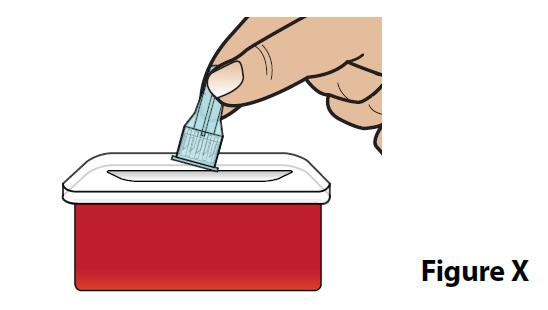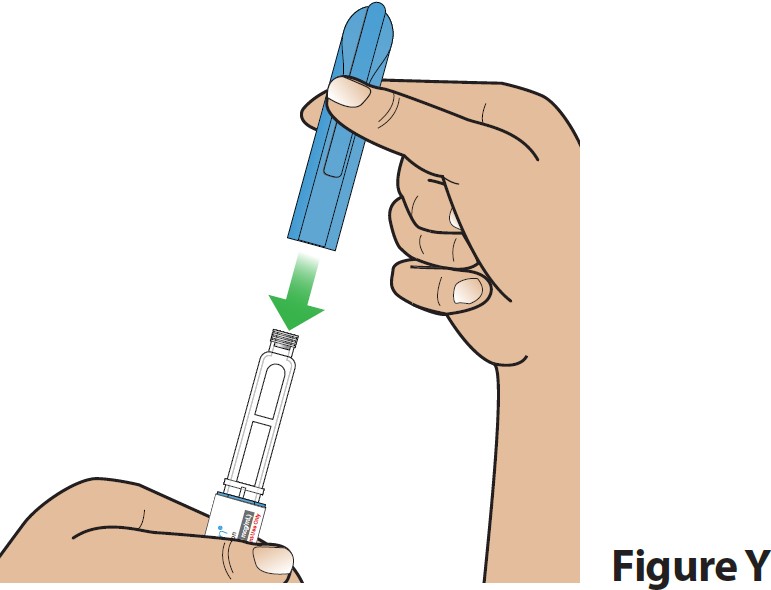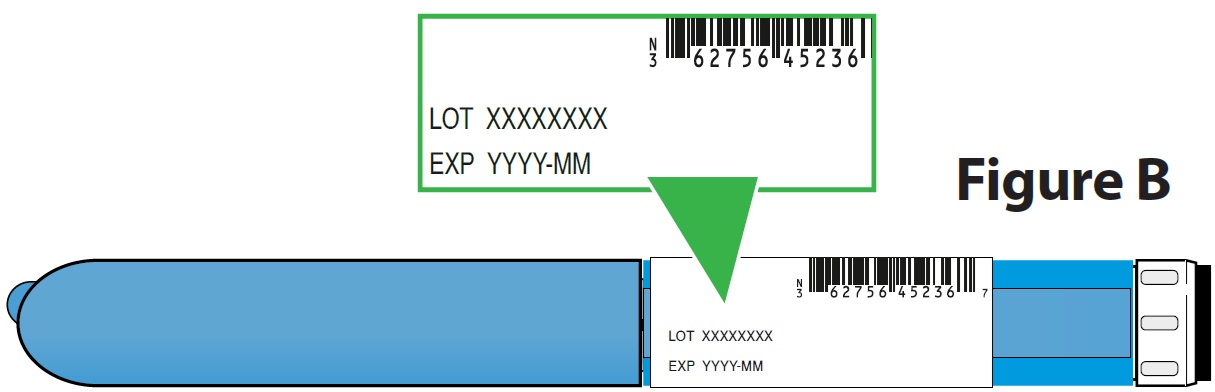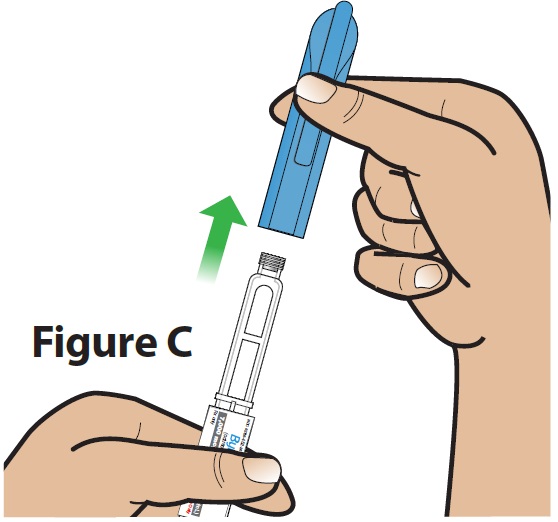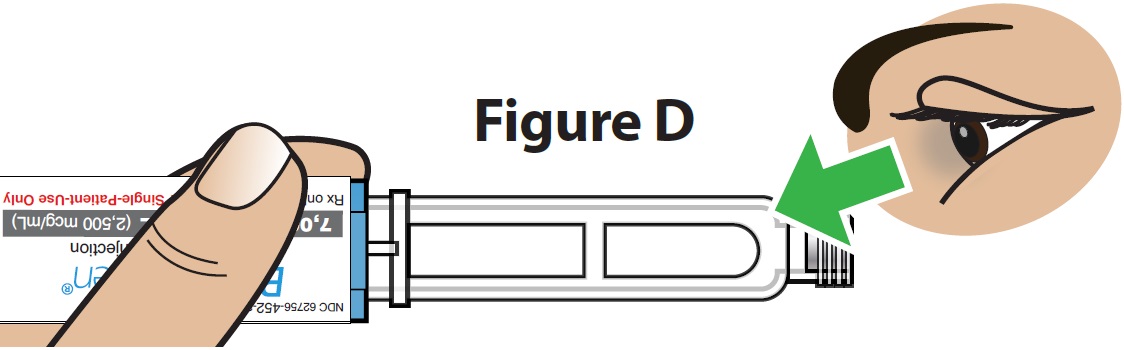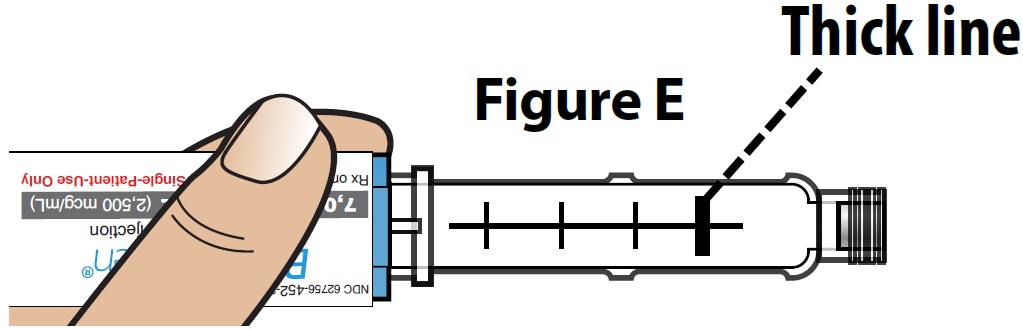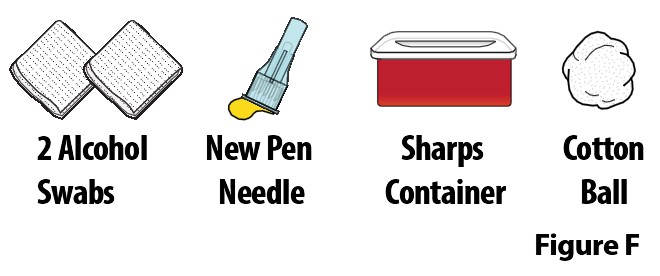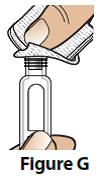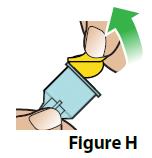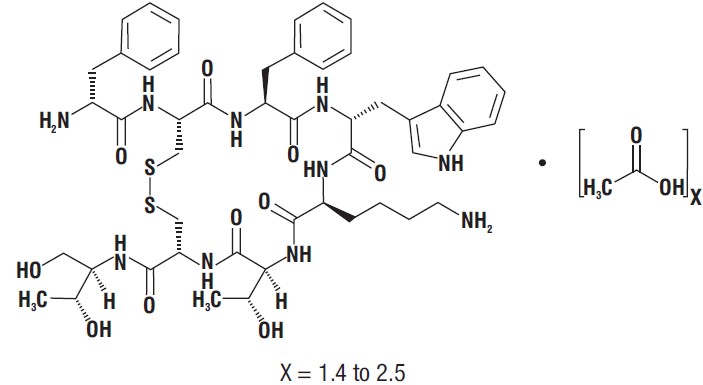 DRUG LABEL: BYNFEZIA Pen
NDC: 62756-452 | Form: INJECTION
Manufacturer: Sun Pharmaceutical Industries, Inc.
Category: prescription | Type: Human Prescription Drug Label
Date: 20250221

ACTIVE INGREDIENTS: OCTREOTIDE ACETATE 2.5 mg/1 mL
INACTIVE INGREDIENTS: LACTIC ACID 3.4 mg/1 mL; MANNITOL 22.5 mg/1 mL; PHENOL 5 mg/1 mL; SODIUM BICARBONATE; WATER

HIGHLIGHTS OF PRESCRIBING INFORMATION

These highlights do not include all the information needed to use BYNFEZIA PEN safely and effectively. See full prescribing information for BYNFEZIA PEN.
BYNFEZIA PEN® (octreotide acetate) injection, for subcutaneous use
Initial U.S. Approval: 1988

1 INDICATIONS AND USAGE

BYNFEZIA PEN is a s o matostatin analogue indicated:

- Acromegaly: To reduce blood levels of growth hormone (GH) and insulin growth factor 1 (IGF-1; somatomedin C) in acromegaly patients who have had inadequate response to or cannot be treated with surgical resection, pituitary irradiation, and bromocriptine mesylate at maximally tolerated doses. (1 .1)
- Carcinoid Tumors: For the symptomatic treatment of patients with m eta static c a rcinoid t u mo rs where it suppresses or inhibits the severe diarrhea and flushing episodes associated with the disease. (1 .2)
- Vasoactive Intestinal Peptide Tumors (VIPomas): For the treatment of profuse watery diarrhea associated with VIP-secreting tumors . (1 .3)

Limitations of Use

Improvement in clinical signs and symptoms, or reduction in tumor size or rate of growth, were not shown in clinical trials performed with octreotide injection; these trials were not optimally designed to detect such effects. (1.4)

2 DOSAGE AND ADMINISTRATION

• BYNFEZIA PEN is administered subcutaneously; alternate injection site periodically (2.1)
• Acromegaly: Recommended initial BYNFEZIA dosage is 50 mcg three times daily during the initial 2 weeks of therapy. Maintenance dose 100 mcg to 500 mcg three times daily. (2.2)
• Carcinoid Tumors: Recommended dosage range of 100 mcg to 600 mcg daily in two to four divided doses during the initial 2 weeks of therapy. (2.3)
• VIPomas: Recommended dosage range of 200 mcg to 300 mcg daily in two to four divided doses during the initial 2 weeks of therapy. (2.4)

3 DOSAGE FORMS AND STRENGTHS

Injection: 7,000 mcg/2.8 mL (2,500 mcg/mL) octreotide (as acetate) in a 2.8 mL single-patient-use prefilled pen (3)

4 CONTRAINDICATIONS

- Sensitivity to this drug or any of the components (4)

5 WARNINGS AND PRECAUTIONS

• Cardiac Conduction Abnormalities: Bradycardia, arrhythmias, or conduction abnormalities may occur. Use with caution in at-risk patients. Dosage adjustment of cardiac medications may be necessary. (5.1)
• Cholelithiasis and Complications of Cholelithiasis: Monitor periodically. Discontinue if complications of cholelithiasis are suspected. (5.2)
• Glucose Metabolism: Hypoglycemia or hyperglycemia may occur. Glucose monitoring is recommended and anti-diabetic treatment may need adjustment. (5.3)
• Thyroid Function: Hypothyroidism may occur. Monitor thyroid levels periodically. (5.4)
• Steatorrhea and Malabsorption of Dietary Fats: New onset steatorrhea, stool discoloration, loose stools, abdominal bloating, and weight loss may occur. If new occurrence or worsening of these symptoms are reported, evaluate for potential pancreatic exocrine insufficiency. (5.5)

6 ADVERSE REACTIONS

Most common adverse reactions (> 10%): (6.1)

- Acromegaly: Gallbladder abnormalities, sinus bradycardia, diarrhea, loose stools nausea, abdominal discomfort, hyperglycemia, and hypothyroidism.
- Carcinoid Tumors and VIPomas: Gallbladder abnormalities.

To report SUSPECTED ADVERSE REACTIONS, contact Sun Pharmaceutical Industries, Inc. at 1-800-818-4555 or FDA at 1-800-FDA-1088 or www.fda.gov/medwatch

7 DRUG INTERACTIONS

- The following drugs require monitoring and possible dose adjustment when used with BYNFEZIA PEN : cyclosporine, insulin, oral hypoglycemic agents, beta-blockers, and bromocriptine. (7)
- Lutetium Lu 177 Dotatate Injection : Discontinue BYNFEZIA PEN at least 24 hours prior to each lutetium Lu 177 dotatate dose. (7.6)

8 USE IN SPECIFIC POPULATIONS

Females and Males of Reproductive Potential: Advise premenopausal females of the potential for an unintended pregnancy. (8.3)

FULL PRESCRIBING INFORMATION

1 INDICATIONS AND USAGE

1.1 Acromegaly

BYNFEZIA PEN is indicated to reduce blood levels of growth hormone (GH) and insulin gro wth factor-1 (I GF-1; somatomedin C) in acromegaly patients who have had inadequate response to or cannot be treated with surgical resection, pituitary irradiation, and bromocriptine mesylate at maximally tolerated doses.

1.2 Carcinoid Tumors

BYNFEZIA PEN is indicated for treat ment of severe diarrhea and flushing episodes associated with metastatic carcinoid tumors.

1.3 Vasoactive Intestinal Peptide Tumors

BYNFEZIA PEN is indicated for the treat ment of the profuse watery diarrhea associated with vasoactive intestinal peptide tumors (VIPomas)-secreting tu mors.

1.4 Important Limitations of Use

Improvement in clinical signs and symptoms, or reduction in tumor size or rate of growth, were not shown in clinical trials performed with octreotide injection; these trials were not optimally designed to detect such effects.

2 DOSAGE AND ADMINISTRATION

2.1 Dosage and Administration Overview

- Inspect visually for particulate matter and discoloration. Only use BYNFEZIA PEN if the solution appears colorless with no visible particles.
- BYNFEZIA PEN should be at room temperature before injecting to reduce potential injection site reactions.
- Administer BYNFEZIA PEN by subcutaneous injection into the abdomen, the front of the middle thighs, or the back/outer area of the upper arms.
- Rotate injection sites so that the same site is not used repeatedly. Injection sites should be at least 2 inches away from your last injection site.
- Provide proper training to patients and/or caregivers on the administration of BYNFEZIA PEN prior to use according to the “Instructions for Use”.

2.2 Recommended Dosage and Monitoring for Acromegaly

The recommended initial dosage of BYNFEZIA PEN is 50 mcg three times daily to be administered subcutaneously. Increase BYNFEZIA dose based upon GH or IGF-1 levels. The goal is to achieve GH levels less than 5 ng/mL or IGF-I levels within normal range. Monitor GH or IGF-1 every two weeks after initiating BYNFEZIA PEN therapy or with dosage change, and to guide titration.

The most common dosage is 100 mcg three times daily, but some patients require up to 500 mcg three times daily for maximum effectiveness. Doses greater than 300 mcg/day seldom result in additional biochemical benefit, and if an increase in dose fails to provide additional benefit, the dose should be reduced.

BYNFEZIA PEN should be withdrawn yearly for approximately 4 weeks from patients who have received irradiation to assess disease activity. If GH or IGF-I levels increase and signs and symptoms recur, BYNFEZIA PEN therapy may be resumed.

2.3 Recommended Dosage and Monitoring for Carcinoid Tumors

The recommended daily dosage of BYNFEZIA PEN during the first 2 weeks of therapy ranges from 100 to 600 mcg/day in two to four divided doses given subcutaneously (mean daily dosage is 300 mcg). In the clinical studies, the median daily maintenance dosage was approximately 450 mcg, but clinical and biochemical benefits were obtained in some patients with as little as 50 mcg, while others required doses up to 1,500 mcg/day. However, experience with doses above 750 mcg/day is limited. Measurement of urinary 5-hydroxyindole acetic acid, plasma serotonin, plasma Substance P may be useful in monitoring the progress of therapy.

2.4 Recommended Dosage and Monitoring for Vasoactive Intestinal Peptide Tumors

Daily dosage of 200 mcg to 300 mcg in two to four divided doses given subcutaneously are recommended during the initial 2 weeks of therapy (range, 150 mcg to 750 mcg) to control symptoms of the disease. On an individual basis, dosage may be adjusted to achieve a therapeutic response; but usually doses above 450 mcg/day are not required. Measurement of Plas ma vasoactive intestinal peptide (VIP) may be useful in monitoring the progress of therapy.

3 DOSAGE FORMS AND STRENGTHS

BYNFEZIA PEN is available as:

- Injection: 7,000 mcg/2.8 mL (2,500 mcg/mL) octreotide (as acetate) as a clear, colorless solution in a single-patient-use prefilled pen.

4 CONTRAINDICATIONS

Sensitivity to this drug or any of its co mponents.

5 WARNINGS AND PRECAUTIONS

5.1 Cardiac Conduction Abnormalities

Cardiac conduction abnormalities have occurred during treatment with octreotide. In acromegalic patients, bradycardia (< 50 bpm) developed in 25%; conduction abnormalities occurred in 10% and arrhythmias occurred in 9% of patients during octreotide therapy [see Adverse Reactions (6)]. Other electrocardiogram (ECG) changes observed included QT prolongation, axis shifts, early repolarization, low voltage, R/S transition, and early R-wave progression. These ECG changes are not uncommon in acromegalic patients. Dose adjustments in drugs such as beta-blockers that have bradycardia effects may be necessary. In one acromegalic patient with severe congestive heart failure (CHF), initiation of octreotide therapy resulted in worsening of CHF with improvement when drug was discontinued. Confirmation of a drug effect was obtained with a positive rechallenge.

5.2 Cholelithiasis and Complications of Cholelithiasis

BYNFEZIA PEN may inhibit gallbladder contractility and decrease bile secretion, which may lead to gallbladder abnormalities or sludge. Acute cholecystitis, ascending cholangitis, biliary obstruction, cholestatic hepatitis, or pancreatitis have been reported with octreotide therapy. In clinical trials (primarily patients with acromegaly or psoriasis), the incidence of biliary tract abnormalities was 63% (27% gallstones, 24% sludge without stones, 12% biliary duct dilatation). The incidence of stones or sludge in patients who received octreotide for 12 months or longer was 52%. Less than 2% of patients treated with octreotide for 1 month or less developed gallstones. One patient developed ascending cholangitis during octreotide therapy and died. If complications of cholelithiasis are suspected, discontinue BYNFEZIA PEN and treat appropriately.

5.3 Hyperglycemia and Hypoglycemia

BYNFEZIA PEN alters the balance between the counter-regulatory hormones, insulin, glucagon and GH, which may result in hypoglycemia or hyperglycemia. The hypoglycemia or hyperglycemia which occurs during octreotide therapy is usually mild but may result in overt diabetes mellitus or necessitate dose changes in insulin or other anti-diabetic agents. Hypoglycemia and hyperglycemia occurred on octreotide in 3% and 16% of acromegalic patients, respectively [see Adverse Reactions (6)]. Severe hyperglycemia, subsequent pneumonia, and death following initiation of octreotide therapy was reported in one patient with no history of hyperglycemia.

Monitor glucose levels during BYNFEZIA PEN therapy. Adjust dosing of insulin or other anti-diabetic therapy accordingly.

5.4 Thyroid Function Abnormalities

Octreotide suppresses secretion of thyroid stimulating hormone (TSH), which may result in hypothyroidism. Baseline and periodic assessment of thyroid function (TSH, total, and/or free T4) is recommended during chronic therapy [see Adverse Reactions (6)].

5.5 Steatorrhea and Malabsorption of Dietary Fats

New onset steatorrhea, stool discoloration and loose stools have been reported in patients receiving somatostatin analogs, including octreotide. Somatostatin analogs reversibly inhibit secretion of pancreatic enzymes and bile acids, which may result in malabsorption of dietary fats and subsequent symptoms of steatorrhea, loose stools, abdominal bloating, and weight loss. If new occurrence or worsening of these symptoms are reported in patients receiving octreotide, evaluate patients for potential pancreatic exocrine insufficiency and manage accordingly.

5.6 Changes in Vitamin B12 Levels

Depressed vitamin B12 levels and abnormal Schilling’s tests have been observed in some patients receiving octreotide therapy and monitoring of vitamin B12 levels is recommended during BYNFEZIA PEN therapy.

6 ADVERSE REACTIONS

The following clinically significant adverse reactions are described elsewhere in the labeling:

- Cardiac Conduction Abnormalities [Warnings and Precautions (5.1)]
- Cholelithiasis and Complications of Cholelithiasis [see Warnings and Precautions (5.2)]
- Hyperglycemia and Hypoglycemia [see Warnings and Precautions (5.3)]
- Thyroid Function Abnormalities [see Warnings and Precautions (5.4)]
- Steatorrhea and Malabsorption of Dietary Fats [see Warnings and Precautions (5.5)]
- Changes in Vitamin B12 Levels [see Warnings and Precautions (5.6)]

6.1 Clinical Trials Experience

Because clinical trials are conducted under widely varying conditions, adverse reaction rates observed in the clinical trials of a drug cannot be directly compared to rates in the clinical trials of another drug and may not reflect the rates observed in practice.

The safety of BYNFEZIA PEN has been established based on clinical studies of octreotide acetate injection. Below is a description of the adverse reactions from the clinical studies.

Gallbladder Abnormalities
Gallbladder abnormalities, especially stones and/or biliary sludge, frequently develop in patients on chronic octreotide therapy [see Warnings and Precautions (5.1)]. In clinical trials (primarily patients with acromegaly or psoriasis) (BYNFEZIA PEN is not indicated for the treatment of psoriasis)], the incidence of biliary tract abnormalities was 63% (27% gallstones, 24% sludge without stones, 12% biliary duct dilatation). The incidence of stones or sludge in patients who received octreotide for 12 months or longer was 52%. Less than 2% of patients treated with octreotide for 1 month or less developed gallstones.
Cardiac
In acromegalics, sinus bradycardia (<50 bpm) developed in 25%; conduction abnormalities occurred in 10% and arrhythmias developed in 9% of patients during octreotide therapy [see Warnings and Precautions (5.1)].

Gastrointestinal
Diarrhea, loose stools, nausea, and abdominal discomfort were each seen in 34% to 61% of acromegalic patients in U.S. studies. 2.6% of the patients discontinued therapy due to these symptoms. These symptoms were seen in 5% to 10% of patients with carcinoid tumors and VIPomas.

The frequency of these symptoms was not dose related, but diarrhea and abdominal discomfort generally resolved more quickly in patients treated with 300 mcg/day than in those treated with 750 mcg/day. Vomiting, flatulence, abnormal stools, abdominal distention, and constipation were each seen in less than 10% of patients.

In rare instances, gastrointestinal side effects may resemble acute intestinal obstruction, with progressive abdominal distension, severe epigastric pain, abdominal tenderness, and guarding.

Hypo/Hyperglycemia
Hypoglycemia and hyperglycemia occurred in 3% and 16% of acromegalic patients, respectively, but only in about 1.5% of other patients. Symptoms of hypoglycemia were noted in approximately 2% of patients.

Hypothyroidism
In acromegalics, biochemical hypothyroidism alone occurred in 12% while goiter occurred in 8% and 4% required initiation of thyroid replacement therapy during octreotide therapy [see Warnings and Precautions (5.4)]. In patients without acromegaly, hypothyroidism has only been reported in several isolated patients and goiter has not been reported.

Other Adverse Events
Pain on injection was reported in 7.7%, headache in 6%, and dizziness in 5%. Pancreatitis was also observed [see Warnings and Precautions (5.2)].

Other Adverse Events 1% to 4%
Other events, each observed in 1% to 4% of patients, included fatigue, weakness, pruritus, joint pain, backache, urinary tract infection, cold symptoms, flu symptoms, injection site hematoma, bruise, edema, flushing, blurred vision, pollakiuria, fat malabsorption, hair loss, visual disturbance, and depression.

Anaphylactoid reactions, including anaphylactic shock, have been reported in several patients receiving octreotide.

6.2 Postmarketing Experience

The following adverse reactions have been identified during postapproval use of octreotide acetate injection. Because these reactions are reported voluntarily from a population of uncertain size, it is not always possible to reliably estimate their frequency or establish a causal relationship to drug exposure.

Hepatobiliary: cholelithiasis, cholecystitis, cholangitis and pancreatitis, which have sometimes required cholecystectomy
Gastrointestinal: intestinal obstruction, pancreatic exocrine insufficiency
Hematologic: thrombocytopenia

7 DRUG INTERACTIONS

7.1 Cyclosporine

Octreotide has been associated with alterations in nutrient absorption, so it may have an effect on absorption of orally administered drugs. Concomitant administration of BYNFEZIA PEN with cyclosporine may decrease blood levels of cyclosporine and result in transplant rejection.

7.2 Insulin and Oral Hypoglycemic Drugs

Octreotide inhibits the secretion of insulin and glucagon. Therefore, blood glucose levels should be monitored when BYNFEZIA PEN treatment is initiated or when the dose is altered and anti-diabetic treatment should be adjusted accordingly.

7.3 Bromocriptine

Concomitant administration of octreotide and bromocriptine increases the availability of bromocriptine.

7.4 Other Concomitant Drug Therapy

Concomitant administration of bradycardia-inducing drugs (e.g., beta-blockers) may have an additive effect on the reduction of heart rate associated with octreotide. Dose adjustments of concomitant medication may be necessary.

Octreotide has been associated with alterations in nutrient absorption, so it may have an effect on absorption of orally administered drugs.

7.5 Drug Metabolism Interactions

Li mited published data indicate that so matostatin analogs might decrease the metabolic clearance of co mpounds known to be metabolized by cytochro me P450 enzy mes, which may be due to the suppression of GH. Since it cannot be excluded that octreotide may have this effect, other drugs mainly metabolized by CYP3A4 and which have a low therapeutic index (e.g., quinidine, terfenadine) should therefore be used with caution.

7.6 Lutetium Lu 177 Dotatate Injection

Octreotide competitively binds to somatostatin receptors and may interfere with the efficacy of lutetium Lu 177 dotatate. Discontinue BYNFEZIA PEN at least 24 hours prior to each lutetium Lu 177 dotatate dose.

8 USE IN SPECIFIC POPULATIONS

8.1 Pregnancy

Risk Summary
The limited data with octreotide acetate in pregnant women are insufficient to inform a drug-associated risk for major birth defects and miscarriage. In animal reproduction studies, no adverse developmental-effects were observed with IV administration of octreotide to pregnant rats and rabbits during organogenesis at doses 7 and 13 times, respectively the maximum recommended human dose (MRHD) of 1.5 mg/day based on body surface area (BSA). Transient growth retardation, with no impact on postnatal development, was observed in rat offspring from a pre- and post-natal study of octreotide at IV doses below the MRHD based on BSA (see Data).

The estimated background risk of major birth defects and miscarriage for the indicated population is unknown. In the U.S. general population, the estimated background risk of major birth defects and miscarriage in clinically recognized pregnancies is 2% to 4% and 15% to 20%, respectively.

Data

Human Data
In postmarketing data, a limited number of exposed pregnancies have been reported in patients with acromegaly. Most women were exposed to octreotide during the first trimester of pregnancy at doses ranging from 100 to 300 mcg/day of octreotide or 20 mg to 30 mg once a month of octreotide acetate for injectable suspension, however some women elected to continue octreotide therapy throughout pregnancy. In cases with a known outcome, no congenital malformations were reported.

Animal Data
In embryo-fetal development studies in rats and rabbits, pregnant animals received IV doses of octreotide up to 1 mg/kg/day during the period of organogenesis. A slight reduction in body weight gain was noted in pregnant rats at 0.1 and 1 mg/kg/day. There were no maternal effects in rabbits or embryo-fetal effects in either species up to the maximum dose tested. At 1 mg/kg/day in rats and rabbits, the dose multiple was approximately 7 and 13 times, respectively, at the highest recommended human dose of 1.5 mg/day based on BSA.

In a pre- and post-natal development rat study at IV doses of 0.02–1 mg/kg/day, a transient growth retardation of the offspring was observed at all doses which was possibly a consequence of GH inhibition by octreotide. The doses attributed to the delayed growth are below the human dose of 1.5 mg/day, based on BSA.

8.2 Lactation

Risk Summary
There is no information available on the presence of octreotide in human milk, the effects of the drug on the breastfed infant, or the effects of the drug on milk production. Studies show that octreotide administered subcutaneously passes into the milk of lactating rats; however, due to species-specific differences in lactation physiology, animal data may not reliably predict drug levels in human milk (see Data). The developmental and health benefits of breastfeeding should be considered along with the mother’s clinical need for BYNFEZIA PEN, and any potential adverse effects on the breastfed child from BYNFEZIA PEN or from the underlying maternal condition.

Data
Following a subcutaneous dose (1 mg/kg) of octreotide to lactating rats, transfer of octreotide into milk was observed at a low concentration compared to plasma (milk/plasma ratio of 0.009).

8.3 Females and Males of Reproductive Potential

Discuss the potential for unintended pregnancy with premenopausal women as the therapeutic benefits of a reduction in GH levels and normalization of insulin-like growth factor 1 (IGF-1) concentration in acromegalic females treated with octreotide may lead to improved fertility.

8.4 Pediatric Use

Safety and efficacy of octreotide injection in the pediatric population have not been demonstrated.

No formal controlled clinical trials have been performed to evaluate the safety and effectiveness of octreotide injection in pediatric patients under age 6 years. In post-marketing reports, serious adverse events, including hypoxia, necrotizing enterocolitis, and death, have been reported with octreotide injection use in children, most notably in children under 2 years of age. The relationship of these events to octreotide has not been established as the majority of these pediatric patients had serious underlying co-morbid conditions.

The efficacy and safety of octreotide injection using the octreotide acetate for injectable suspension formulation was examined in a single randomized, double-blind, placebo-controlled, 6 month pharmacokinetics study in 60 pediatric patients age 6 to 17 years with hypothalamic obesity resulting from cranial insult. The mean octreotide concentration after 6 doses of 40 mg octreotide acetate for injectable suspension administered by intramuscular (IM) injection every 4 weeks was approximately 3 ng/mL. Steady-state concentrations was achieved after 3 injections of a 40 mg dose. Mean body mass index (BMI) increased 0.1 kg/m^2 in octreotide acetate for injectable suspension-treated subjects compared to 0.0 kg/m^2 in saline control-treated subjects. Efficacy was not demonstrated. Diarrhea occurred in 11 of 30 (37%) patients treated with octreotide acetate for injectable suspension. No unexpected adverse events were observed. However, with octreotide acetate for injectable suspension at 40 mg once a month, the incidence of new cholelithiasis in this pediatric population (33%) was higher than that seen in other adult indications such as acromegaly (22%) or malignant carcinoid syndrome (24%), where octreotide acetate for injectable suspension was 10 mg to 30 mg once a month.

8.5 Geriatric Use

Clinical studies of octreotide did not include sufficient numbers of subjects aged 65 and over to determine whether they respond differently from younger subjects. Other reported clinical experience has not identified differences in responses between the elderly and younger patients. In general, dose selection for an elderly patient should be cautious, usually starting at the low end of the dosing range, reflecting the greater frequency of decreased hepatic, renal, or cardiac function, and of concomitant disease or other drug therapy.

8.6 Renal Impairment

In patients with severe renal failure requiring dialysis, the half-life of octreotide may be increased, necessitating adjustment of the maintenance dosage [see Clinical Pharmacology (12.3)].

8.7 Hepatic Impairment-Cirrhotic Patients

In patients with liver cirrhosis, the half-life of the drug may be increased, necessitating adjustment of the maintenance dosage [see Clinical Pharmacology (12.3)].

10 OVERDOSAGE

A limited number of accidental overdoses of octreotide in adults have been reported. In adults, the doses ranged from 2,400 to 6,000 mcg/day administered by continuous infusion (100 to 250 mcg/hour) or subcutaneously (1,500 mcg 3 times a day). Adverse events in some patients included arrhythmia, hypotension, cardiac arrest, brain hypoxia, pancreatitis, hepatitis steatosis, hepatomegaly, lactic acidosis, flushing, diarrhea, lethargy, weakness, and weight loss.

If overdose occurs, symptomatic management is indicated. Up-to-date information about the treatment of overdose can often be obtained from the National Poison Control Center at 1-800-222-1222.

11 DESCRIPTION

BYNFEZIA PEN (octreotide acetate) injection contains octreotide as its acetate salt. Octreotide is a somatostatin analogue. Octreotide acetate known chemically as L-Cysteinamide, D-phenylalanyl-L-cysteinyl-L-phenylalanyl-D-tryptophyl-L-lysyl-L-threonyl-N-[2-hydroxy-1-(hydroxymethyl)propyl]-, cyclic (2→7)-disulfide; [R-(R*, R*)] acetate salt.

The molecular formula of octreotide free base is C49H66N10O10S2 and its molecular weight is 1019.3 and its structural formula as acetate salt is:

BYNFEZIA PEN (octreotide acetate) injection is available as a disposable single-patient-use prefilled pen containing 7,000 mcg of octreotide (as acetate)/2.8 mL. Each milliliter of octreotide acetate injection contains 2,500 mcg octreotide (present as octreotide acetate, USP), 3.4 mg lactic acid, 22.5 mg mannitol, 5 mg phenol, and Water for Injection (q.s.). The pH of the solution is adjusted to 4.2 ± 0.3 by the addition of aqueous sodium bicarbonate solution.

12 CLINICAL PHARMACOLOGY

12.1 Mechanism of Action

BYNFEZIA PEN (octreotide acetate) exerts pharmacologic actions similar to the natural hormone, somatostatin. It is an even more potent inhibitor of GH, glucagon, and insulin than somatostatin. Like somatostatin, it also suppresses luteinizing hormone (LH) response to gonadotropin releasing hormone (GnRH), decreases splanchnic blood flow, and inhibits release of serotonin, gastrin, VIP, secretin, motilin, and pancreatic polypeptide.

By virtue of these pharmacological actions, octreotide has been used to treat the symptoms associated with metastatic carcinoid tumors (flushing and diarrhea), and VIP secreting adenomas (watery diarrhea).

12.2 Pharmacodynamics

Octreotide substantially reduces GH and/or IGF-I (somatomedin C) levels in patients with acromegaly.

Single doses of octreotide have been shown to inhibit gallbladder contractility and to decrease bile secretion in normal volunteers. In controlled clinical trials, the incidence of gallstone or biliary sludge formation was markedly increased [see Warnings and Precautions (5.2)].

Octreotide suppresses secretion of TSH.

12.3 Pharmacokinetics

Absorption

After subcutaneous injection, octreotide is absorbed rapidly and co mpletely from the injection site. Peak concentrations of 5.2 ng/ mL (100 mcg dose) were reached 0.4 hours after dosing. Peak concentrations and area under the curve (AUC) values were dose proportional after subcutaneous single doses up to 500 mcg and after subcutaneous multiple doses up to 500 mcg 3 times a day (1,500 mcg/day). In patients with acromegaly, a mean peak concentration of 2.8 ng/mL (100 mcg dose) was reached in 0.7 hours after subcutaneous dosing.

Distribution

In healthy volunteers, the distribution of octreotide from plas ma was rapid (tα1/2 = 0.2 h), the volu me of distribution (Vdss) was esti mated to be 13.6 L, and the total body clearance ranged from 7 L/hr to 10 L/hr. In blood, the distribution into the erythrocytes was found to be negligible and about 65% was bound in the plas ma in a concentration-independent manner. Binding was mainly to lipoprotein and, to a lesser extent, to albu min. In patients with acromegaly, the volume of distribution (Vdss) was estimated to be 21.6 ± 8.5 L, and the total body clearance was increased to 18 L/h. The mean percent of the drug bound was 41.2%.

Elimination

The eli mination of octreotide from plas ma had an apparent half-life of 1.7 to 1.9 hours co m pared with 1 to 3 minutes with the natural hor mone. The duration of action of octreotide injection is variable but extends up to 12 hours depending upon the type of tu mor. About 32% of the dose is excreted unchanged into the urine. In an elderly population, dose adjustments may be necessary due to a significant increase in the half-life (46%) and a significant decrease in the clearance (26%) of the drug.

In patients with acromegaly, the disposition and elimination half-lives were similar to normal subjects.

Specific Populations

Renal Impairment

In patients with mild renal i mpair ment (C LCR 40 to 60 m L/ min), octreotide t1/2 was 2.4 hours and total body clearance was 8.8 L/hr, in moderate i mpair ment (CLCR 10 to 39 m L/ min) t1/2 was 3.0 hours and total body clearance 7.3 L/hr. In patients with severe renal i mpairment not requiring dialysis (CLCR <10 m L/ min), octreotide t1/2 was 3.1 hours and total body clearance was 7.6 L/hr. In patients with severe renal failure requiring dialysis, total body clearance was reduced to about half that found in healthy subjects (from approximately 10 L/hr to 4.5 L/hr).

Hepatic Impairment

Patients with liver cirrhosis showed prolonged elimination of drug, with octreotide t1/2 increasing to 3.7 hr and total body clearance decreasing to 5.9 L/hr, whereas patients with fatty liver disease showed t1/2 increased to 3.4 hr and total body clearance of 8.2 L/hr.

12.6 Immunogenicity

Evaluation of 20 patients treated for at least 6 months has failed to demonstrate titers of antibodies exceeding background levels. However, antibody titers to octreotide injection were subsequently reported in 3 patients and resulted in prolonged duration of drug action in 2 patients.

13 NONCLINICAL TOXICOLOGY

13.1 Carcinogenesis, Mutagenesis, Impairment of Fertility

Studies in laboratory animals have demonstrated no mutagenic potential of octreotide injection.

No carcinogenic potential was demonstrated in mice treated subcutaneously for 85 to 99 weeks at doses up to 2,000 mcg/kg/day (8 x the human exposure based on BSA). In a 116-week subcutaneous study in rats, a 27% and 12% incidence of injection-site sarcomas or squamous cell carcinomas was observed in males and females, respectively, at the highest dose level of 1,250 mcg/kg/day (10 x the human exposure based on BSA) compared to an incidence of 8% to 10% in the vehicle-control groups. The increased incidence of injection site tumors was most probably caused by irritation and the high sensitivity of the rat to repeated subcutaneous injections at the same site. Rotating injection sites would prevent chronic irritation in humans. There have been no reports of injection-site tumors in patients treated with octreotide for up to 5 years. There was also a 15% incidence of uterine adenocarcinomas in the 1,250 mcg/kg/day females compared to 7% in the saline-control females and 0% in the vehicle-control females. The presence of endometritis coupled with the absence of corpora lutea, the reduction in mammary fibroadenomas, and the presence of uterine dilatation suggest that the uterine tumors were associated with estrogen dominance in the aged female rats which does not occur in humans.

Octreotide did not impair fertility in rats at doses up to 1,000 mcg/kg/day, which represents 7 times the human exposure based on BSA.

16 HOW SUPPLIED/STORAGE AND HANDLING

How Supplied

BYNFEZIA PEN (octreotide acetate) injection, 7,000 mcg/2.8 mL (2,500 mcg /mL) octreotide is a clear colorless solution and it is available as:

Dosage Unit | Package Size | NDC #
2.8 mL single -patient-use prefilled pen | Carton of 1 | NDC 62756-452-36
2.8 mL single -patient-use prefilled pen | Carton of 2 | NDC 62756-452-37

Dispense in the original sealed carton with the enclosed Instructions for Use.

Storage and Handling

Before first use, store BYNFEZIA PEN in the refrigerator between 2°C to 8°C (36°F to 46°F) and store in outer carton in order to protect from light. After first use, store pens at controlled room temperature between 20°C to 25°C (68°F to 77°F). Excursions between 15°C (59°F) and 30°C (86°F) are allowed for up to 28 days. Discard the pen 28 days after first use. Do not freeze.

17 PATIENT COUNSELING INFORMATION

Advise patient and/or caregivers to read the FDA-approved patient labeling (Instructions for Use).

Sterile Subcutaneous Injection Technique

Careful instruction in sterile subcutaneous injection technique should be given to the patients and to other persons who may administer BYNFEZIA PEN.

Cholelithiasis and Complications of Cholelithiasis

Advise patients to contact their healthcare provider if they experience signs or symptoms of gallstones (cholelithiasis) or complications of cholelithiasis (e.g., cholecystitis, cholangitis, and pancreatitis) [see Warnings and Precautions (5.2)].

Steatorrhea and Malabsorption of Dietary Fats

Advise patients to contact their healthcare provider if they experience new or worsening of steatorrhea, stool

discoloration, loose stools, abdominal bloating, and weight loss [see Warnings and Precautions (5.5)].

Pregnancy

Inform female patients that treatment with BYNFEZIA PEN may result in unintended pregnancy [see Use in Specific Populations (8.3)].

All trademarks are the property of their respective owners.

Distributed by:

Sun Pharmaceutical Industries, Inc.

Cranbury, NJ 08512

Manufactured by:
Sun Pharmaceutical Industries Ltd., India
At M/s. OneSource Specialty Pharma Limited
Plot No. 2-D1, Obadenahalli,
Doddaballapura, 3rd Phase,
Industrial Area, Doddaballapura Taluk,
Bengaluru Rural, 561203, Karnataka INDIA

INSTRUCTIONS FOR USE

BYNFEZIA PEN® (ben-FEZ-ee-uh PEN)

(octreotide acetate) Prefilled Pen

Read these instructions before you start using the BYNFEZIA PEN. It is important that you understand and follow these instructions to use the pen correctly. BYNFEZIA PEN is a prefilled pen that you or your caregiver can use to give more than 1 dose of medicine.
Ask your healthcare provider about your dose of BYNFEZIA PEN and how to inject BYNFEZIA PEN the right way before you inject it for the first time. If your healthcare provider decides that you or your caregiver can give your BYNFEZIA PEN at home, you or your caregiver should receive training on how to use the pen.
Contact your healthcare provider if you or your caregiver have any questions.

Important

• Do not use a pen for more than 28 days after first use. After 28 days throw away (dispose of) the pen, even if the pen still has medicine in it.
• Do not place the pen in water or any other liquid.
• Keep your pen and needles out of the reach of children.
• Do not use if any part of your pen appears broken or damaged.
• If you drop your pen, prime it before you use it again to make sure the pen still works correctly (see step 3. Prime Your Pen).
• Do not take BYNFEZIA PEN solution out of the pen and put it into a syringe.
• Do not share your pen or needles with another person. You may give an infection to them or get an infection from them.
• Do not remove the outer needle cover or inner needle cover until you are ready to inject.
• Do not press the injection button unless a needle is attached to the pen.

How should I store my BYNFEZIA PEN?

Before First Use:
• Store new unused pens in the refrigerator between 36°F to 46°F (2°C to 8°C) and store in the outer carton in order to protect from light.
• Do not freeze. Throw away (dispose of) the pen if it has been frozen.
• Do not store the pen in direct sunlight.
After First Use or During Use:
• Store the pen at room temperature between 68°F to 77°F (20°C to 25°C) for up to 28 days.
• Store the pen with the pen cap on.
• Throw away (dispose of) the pen 28 days after first use in a sharps container, even if the pen still has medicine in it (see step 6. Additional Disposal Information).
• Do not store a pen with a needle attached.

How do I give a dose larger than 200 mcg (more than 1 injection)?

1. Turn the dose set knob to 200 mcg (highest dose setting) and give the first injection. Choose a different injection site for each injection at least 2 inches from the area you used for your last injection.
2. Calculate the remaining dose by subtracting 200 mcg from the prescribed dose.
3. Turn the dose set knob to the line for your remaining dose up to the highest dose setting of 200 mcg. Give the second injection at least 2 inches away from the first injection.
4. You may need more injections to give your total prescribed dose (see examples below).
See the following examples to give a total dose larger than 200 mcg:

Example Dose

Steps to give a total dose larger than 200 mcg

Number of injections needed to give the total dose

For example, if your total dose is 300 mcg

1. Turn the dose set knob to 200 mcg for your first injection.
2. Your remaining dose is 100 mcg.
3. For the second injection, turn your dose set knob to 100 mcg to give the remaining dose.

2

For example, if your total dose is 450 mcg

1. Turn the dose set knob to 200 mcg for your first injection.
2. Your remaining dose is 250 mcg.
3. Turn the dose set knob to 200 mcg for your second injection.
4. Your remaining dose is 50 mcg.
5. For the third injection, turn your dose set knob to 50 mcg to give the remaining dose.

3

1. Check the Pen

A. Wash your hands with soap and water (Figure A).

B. Check the expiration (EXP) date (Figure B).

- Check the pen label to make sure the expiration date has not passed.

Do not use if the expiration date has passed.

C. Pull the pen cap straight off the pen (Figure C).

D. Check the medicine (Figure D).

- The medicine should be clear and colorless. You may see small air bubbles in the pen, which is normal and will not affect the dose.

Do not use if the medicine looks cloudy, colored, or has lumps or particles in it. The pen cartridge may look empty because the medicine is clear and colorless.

- Make sure you have enough medicine left in the pen to inject the full dose. When the plunger moves pass the thick line, your pen is almost empty (Figure E). If the dose set knob does not let you dial your prescribed dose, this means there is not enough medicine left in your pen. Throw away (dispose of) the pen and use a new pen for the injection.

E. Allow the pen to reach room temperature.

- If the pen was not stored at room temperature between 68°F to 77°F (20°C to 25°C), allow it to reach room temperature for 20 to 30 minutes before injecting. This will reduce the chance of getting a reaction at the injection site.

Do not try to warm the pen by using a heat source such as hot water or microwave.

- See the section "How should I store my BYNFEZIA PEN ?" for more information.

2. Attach a Needle

A. Gather the following additional supplies (Figure F):

- 2 alcohol swabs
- new pen needle
- sharps container
- cotton ball

Note: These supplies are not included with the pen.

B. Wipe the rubber seal on the pen with an alcohol swab (Figure G).

C. Attach a new needle.

- Use only 31 gauge, 5 mm length disposable pen needles. If you have questions about which needle to use, ask your healthcare provider.
- Peel off the paper tab from the needle (Figure H).
- Push the needle with cap straight down onto the pen and screw it on to the pen by turning to the right (clockwise) until the needle feels secure (Figure I).

Do not overtighten the needle. This will make it hard to remove after the injection.

D. Remove the outer needle cover and set it aside (Figure J).

- Save the outer needle cover for use when you remove the needle in step 6.

E. Remove the inner needle cover and throw it away (Figure K).

Are you using a new pen?

- If Yes, complete step 3.
- If No, skip step 3 and go to step 4.

3. Prime Your Pen

Note: The following steps are only needed if you are using a new pen for the first time or if you drop the pen.
To prime the pen, follow the steps below to dial the pen to 100 mcg and press the injection button until a stream of medicine comes from the needle tip.

- If you have already primed the pen, go to step 4 to prepare and give the injection.
- Do not prime the pen before each dose. This will waste medicine.

A. Turn the dose set knob to dial the pen to 100 mcg (Figure L).

B. Hold the pen with the needle pointing up.

C. Press the injection button all the way in until it stops and the dose display window returns to “0” (Figure M).

D. A stream of medicine should be seen coming from the needle tip (Figure N).
If you do not see a stream of medicine coming from the needle tip, repeat the priming steps.
If you still do not see a stream of medicine coming from the needle tip after you repeat the priming steps 3 times, the pen may be damaged. Throw away (dispose of) the pen and use a new pen. Call Sun Pharmaceutical Industries, Inc. at 1-800-818-4555or your healthcare provider for help or to get a new pen.

4. Prepare the Injection

A. Choose an injection site (see Figure O) for injection under the skin (subcutaneous).

- When giving yourself the injection: Inject into the stomach at least 2 inches away from the belly button (navel) or inject into the front of the middle thighs (Figure O).
- When giving someone else the injection: you may also inject into the back outer area of the upper arms (Figure O).
- Always change (rotate) the injection site with each injection. Your injection site should be at least 2 inches away from your last injection site.

Do not inject into moles, scars, birthmarks, or areas where the skin is tender, bruised, red, or hard.

B. Clean your injection site with an alcohol swab (Figure P).

- Wipe the skin with an alcohol swab. Let the injection site dry before you inject your dose.

C. Dial your dose (Figure Q).

- Turn the dose set knob until you see the prescribed dose in the dose display window. The dose number and black line should line up with the pointer. The pen can be used to deliver 50 mcg, 100 mcg, 150 mcg and 200 mcg doses.

If your prescribed dose is more than 200 mcg, see the section “How should I give a dose larger than 200 mcg (more than 1 injection)?” in these instructions.

- It is normal to hear a “clicking” sound as you turn the dose set knob.
- If you accidentally dial past the prescribed dose, turn the dose set knob back down to the correct dose.

Note: The pen cannot be dialed past the number of micrograms (mcgs) of medicine left in the pen. If the pen does not have enough medicine to give the full dose, throw away (dispose of) the pen and use a new one.

5. Give the Injection

A. Insert the needle straight into the injection site (Figure R).

B. Deliver your dose.

- Deliver your dose by slowly pressing the injection button all the way down until it stops. The number in the dose display window will go back to “0” when the injection is complete (Figure S).

C. Continue to hold the injection button down and slowly count to 10 to make sure the full dose of medicine is given (Figure T).

D. Remove the pen from the injection site.

- Lift the pen straight up from the injection site (Figure U).
- If you see 1 or 2 drops of medicine on the needle tip, this is normal and will not affect your dose.
- If you see more than 2 drops of medicine on the needle tip, or you see liquid around the injection site after your injection, you may not have received your full dose.

If this happens: Do not inject another dose. Contact your healthcare provider for help. Next time you inject, make sure to keep the pen needle in your skin and continue to hold the injection button down while slowly counting to 10 (see Figure T).
Note: As the pen is used, a plunger will appear in the cartridge and move towards the thick line.

6. After the Injection

A. Carefully place the outer needle cover back onto the needle.

- Place the outer needle cover on a flat surface. Hold the syringe with the needle attached in 1 hand and carefully slip the needle into the outer needle cover without using the other hand. Push the outer needle cover completely on (Figure V).

Do not recap with the inner needle cover.

B. Unscrew and remove the covered needle (Figure W).

- Squeeze the lower part of the covered needle while turning it to the left (counter clockwise).
- Keep turning until the covered needle lifts away from the pen. It may take several turns for the covered needle to lift away from the pen.

C. Throw away (dispose of) the covered needle in a FDA-cleared sharps container (Figure X).

D. Put the pen cap back on the pen (Figure Y) and store the pen.

- After use, store pens with the cap on at room temperature between 68°F to 77°F (20°C to 25°C) or in the refrigerator between 36°F to 46°F (2°C to 8°C) for up to 28 days.
- See the section "How should I store my BYNFEZIA PEN?" for more information on storing your pen.

E. Treat the injection site.

- If needed, press the injection site lightly with a cotton ball or an alcohol swab. Do not rub the area.

Cleaning the Pen

- Wipe the outside of the pen with a clean, damp cloth.
- White particles may appear on the outside tip of the cartridge during normal use. You may remove them with an alcohol swab.
- Do not put the pen in water or any other liquid.

Additional Disposal Information

Put used pens and needles in a FDA-cleared sharps disposal container right away after use. Do not throw away (dispose of) pens and needles in the household trash.
If you do not have a FDA-cleared sharps disposal container, you may use a household container that is:

- made of a heavy-duty plastic,
- can be closed with a tight-fitting, puncture-resistant lid, without sharps being able to come out,
- upright and stable during use,
- leak-resistant, and
- properly labeled to warn of hazardous waste inside the container.

When your sharps disposal container is almost full, you will need to follow your community guidelines for the right way to dispose of your sharps disposal container. There may be state or local laws about how you should throw away used needles and syringes. For more information about safe sharps disposal, and for specific information about sharps disposal in the state that you live in, go to the FDA's website at: http://www.fda.gov/safesharpsdisposal

- Do not dispose of your used sharps disposal container in your household trash unless your community guidelines permit this.
- Do not recycle your used sharps disposal container.
- Always keep the sharps disposal container out of the reach of children and pets.

This Instructions for Use has been approved by the U.S. Food and Drug Administration.
All trademarks are the property of their respective owners.

Distributed by:

Sun Pharmaceutical Industries, Inc.

Cranbury, NJ 08512

Manufactured by:
Sun Pharmaceutical Industries Ltd., India
At M/s. OneSource Specialty Pharma Limited
Plot No. 2-D1, Obadenahalli,
Doddaballapura, 3rd Phase,
Industrial Area, Doddaballapura Taluk,
Bengaluru Rural, 561203, Karnataka INDIA

For more information, call 1-800-818-4555.

Issued: 10/2024

PACKAGE LABEL.PRINCIPAL DISPLAY PANEL

Rx only
NDC 62756-452-37
Bynfezia Pen® (octreotide acetate Injection)
7,000 mcg/2.8mL (2,500 mcg/mL)
Two 2.8 mL disposable single-patient-use prefilled pens
Subcutaneous use only
For doses of 50 mcg, 100 mcg, 150 mcg, and 200 mcg of octreotide per injection.
For Single Patient Use Only
Dispense in this sealed carton
SUN PHARMA